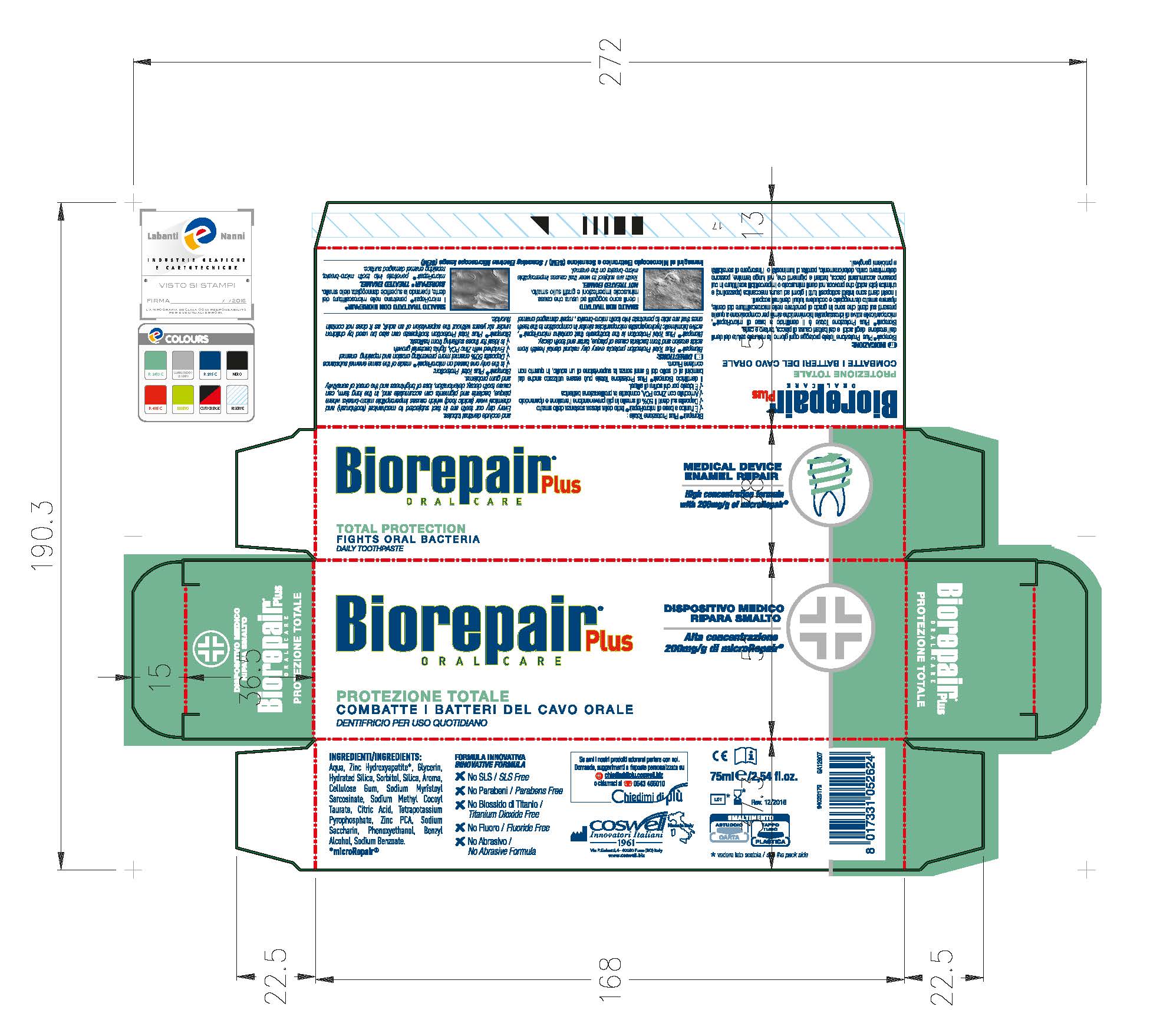 DRUG LABEL: Biorepair Total Protection
NDC: 70781-007 | Form: PASTE
Manufacturer: Coswell Spa
Category: otc | Type: HUMAN OTC DRUG LABEL
Date: 20170613

ACTIVE INGREDIENTS: DIBASIC CALCIUM PHOSPHATE DIHYDRATE 15.11 g/100 g
INACTIVE INGREDIENTS: BENZYL ALCOHOL; PHENOXYETHANOL; SACCHARIN SODIUM; SODIUM BENZOATE; CARBOXYMETHYLCELLULOSE SODIUM; GLYCERIN; WATER; SORBITOL; HYDRATED SILICA; SODIUM LAURYL SULFATE; SILICON DIOXIDE; POTASSIUM PYROPHOSPHATE; SODIUM MYRISTOYL SARCOSINATE; SODIUM METHYL COCOYL TAURATE; CITRIC ACID MONOHYDRATE; ZINC PIDOLATE

ACTIVE INGREDIENT

Contains:

Dicalcium Phosphate Dihyrate (0.5109 fl.oz)

Inactive Ingredients:

Aqua, Glycerin, Hydrated Silica, Sorbitol, Silica, Aroma, Cellulose Gum, Sodium Myristoyl Sarcosinate, Sodium Methyl Cocyl Taurate, Citric Acid, Tetrapotassium Pyrophosphate, Zinc PCA, Sodium Saccharin, Benzyl Alcohol, Phenoxtethanol, Sodium Benzoate

PURPOSE

Biorepair Plus Total Protection protects every day natural dental health from acids erosion and from bacteria cause of plaque, tartar and tooth decay.

Biorepair Plus Total Protection is the toothpaste that contains microRepair active biomimetic hydroxyapatite microparticles similar in composition to teeth ones that are able to penetrate into tooth micro-breaks, repair damaged enamel and occude dentinal tubules

KEEP OUT OF REACH OF CHILDREN

Biorepair Plus Total Protection toothpaste can also be use by children under six years without the supervision of an adult, as it does not contain fluride

DOSAGE AND ADMINISTRATION

For daily usage.

For daily usage.

Warnings